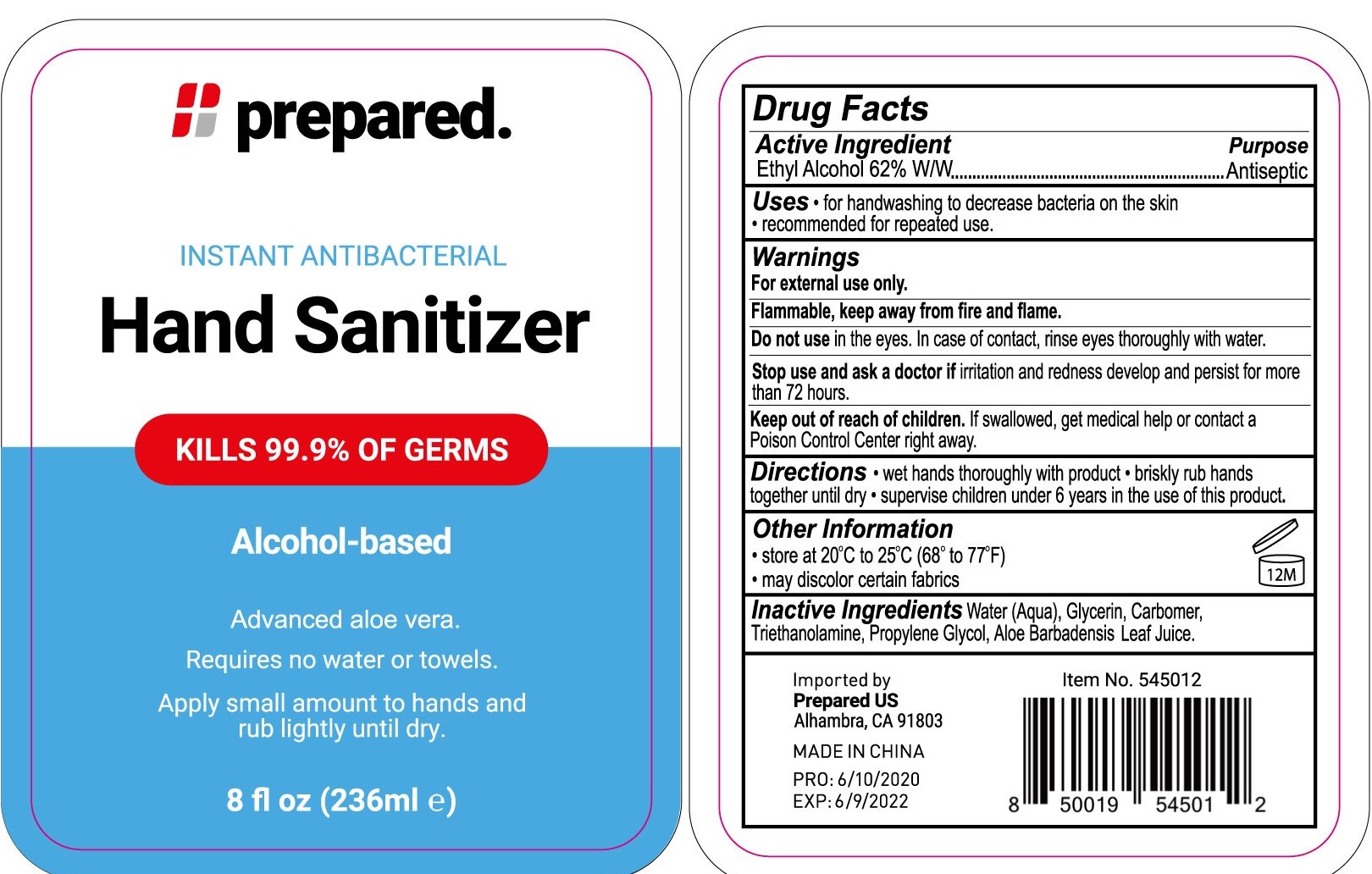 DRUG LABEL: Prepared Instant Antibacterial Hand Sanitizer
NDC: 74149-018 | Form: GEL
Manufacturer: Yiwu Yangjie Daily Chemicals Co.,Ltd.
Category: otc | Type: HUMAN OTC DRUG LABEL
Date: 20200603

ACTIVE INGREDIENTS: alcohol 62 mL/100 mL
INACTIVE INGREDIENTS: WATER; PROPYLENE GLYCOL; ALOE VERA LEAF; GLYCERIN; TROLAMINE

Drug facts

Active ingredient - Ethyl Alcohol 62% W/W

Purpose - Antiseptic

KEEP OUT OF REACH OF CHILDREN

If swallowed, get medical help or contact a poison control center right away.

USES:

- For handwashing to decrease bacteria on the hands
- Recommended for repeated use

WARNINGS

For external use only.
Flammable. Keep away from fire or flame.

Do not use in the eyes. In case of contact, rinse eyes thoroughly with water.

Stop use and ask a doctor If irritation and redness develops and persist for more than 72 hours.

Directions:

- Wet hands thoroughly with product
- briskly rub hands together until dry
- spervise children uder 6 years in the ue of this product.

Other information:

- Store at20℃ to 25℃ (68℉ to 77℉)
- may discolor certain fabrics

INACTIVE INGREDIENT

Water (Aqua), Glycerin, Carbomer, Triethanolamine, Propylene Glycol, Aloe Barbadensis Leaf Juice.